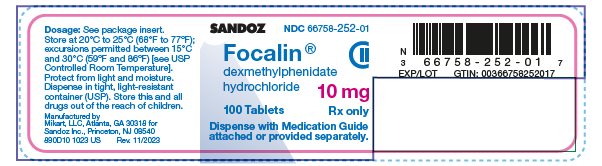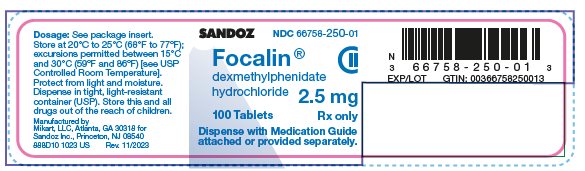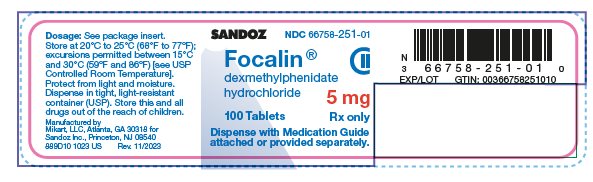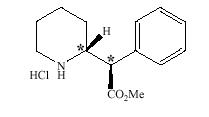 DRUG LABEL: Focalin
NDC: 66758-250 | Form: TABLET
Manufacturer: Sandoz Inc
Category: prescription | Type: HUMAN PRESCRIPTION DRUG LABEL
Date: 20240530
DEA Schedule: CII

ACTIVE INGREDIENTS: DEXMETHYLPHENIDATE HYDROCHLORIDE 2.5 mg/1 1
INACTIVE INGREDIENTS: FD&C BLUE NO. 1; LACTOSE MONOHYDRATE; MAGNESIUM STEARATE; MICROCRYSTALLINE CELLULOSE; STARCH, CORN; SODIUM STARCH GLYCOLATE TYPE A POTATO

HIGHLIGHTS OF PRESCRIBING INFORMATION

These highlights do not include all the information needed to use FOCALIN safely and effectively. See full prescribing information for FOCALIN.
FOCALIN® (dexmethylphenidate hydrochloride) tablets, for oral use, CII
Initial U.S. Approval: 2001

RECENT MAJOR CHANGES

Boxed Warning 10/2023

Dosage and Administration (2.1, 2.2) 10/2023

Warnings and Precautions (5.1, 5.2, 5.8, 5.9, 5.10) 10/2023

WARNING: ABUSE, MISUSE, AND ADDICTION

See full prescribing information for complete boxed warning.

Focalin has a high potential for abuse and misuse, which can lead to the development of a substance use disorder, including addiction. Misuse and abuse of CNS stimulants, including Focalin, can result in overdose and death (5.1, 9.2, 10):

- Before prescribing Focalin, assess each patient’s risk for abuse, misuse, and addiction.
- Educate patients and their families about these risks, proper storage of the drug, and proper disposal of any unused drug.
- Throughout treatment, reassess each patient’s risk and frequently monitor for signs and symptoms of abuse, misuse, and addiction.

1 INDICATIONS AND USAGE

Focalin is a central nervous system (CNS) stimulant indicated for the treatment of Attention Deficit Hyperactivity Disorder (ADHD) (1).

2 DOSAGE AND ADMINISTRATION

- Administer orally twice daily, 4 hours apart with or without food (2).
- For patients new to methylphenidate: Recommend starting dose of 5 mg once daily (2.5 mg twice daily) (2.2).
- For patients currently taking methylphenidate: Initiate Focalin therapy with half (1/2) the current total daily dose of methylphenidate (2.2).
- Titrate weekly in increments of 2.5 to 5 mg to a maximum of 20 mg/day (10 mg twice daily) (2.2).

3 DOSAGE FORMS AND STRENGTHS

Tablets: 2.5 mg, 5 mg, and 10 mg (3).

4 CONTRAINDICATIONS

- Known hypersensitivity to methylphenidate or other components of Focalin (4).
- Concurrent treatment with a monoamine oxidase inhibitor (MAOI), or use of an MAOI within the preceding 14 days (4).

5 WARNINGS AND PRECAUTIONS

- Risks to Patients with Serious Cardiac Disease: Avoid use in patients with known structural cardiac abnormalities, cardiomyopathy, serious cardiac arrhythmias, coronary artery disease, or other serious cardiac disease (5.2).
- Increased Blood Pressure and Heart Rate: Monitor blood pressure and pulse (5.3).
- Psychiatric Adverse Reactions: Prior to initiating Focalin, screen patients for risk factors for developing a manic episode. If new psychotic or manic symptoms occur, consider discontinuing Focalin (5.4).
- Priapism: If abnormally sustained or frequent and painful erections occur, patients should seek immediate medical attention (5.5).
- Peripheral Vasculopathy, including Raynaud’s Phenomenon: Careful observation for digital changes is necessary during Focalin treatment. Further clinical evaluation (e.g., rheumatology referral) may be appropriate for patients who develop signs or symptoms of peripheral vasculopathy (5.6).
- Long-Term Suppression of Growth in Pediatric Patients: Closely monitor growth (height and weight) in pediatric patients. Pediatric patients not growing or gaining height or weight as expected may need to have their treatment interrupted (5.7).
- Acute Angle Closure Glaucoma: Focalin -treated patients considered at risk for acute angle closure glaucoma (e.g., patients with significant hyperopia) should be evaluated by an ophthalmologist (5.8).
- Increased Intraocular Pressure (IOP) and Glaucoma: Prescribe Focalin to patients with open-angle glaucoma or abnormally increased IOP only if the benefit of treatment is considered to outweigh the risk. Closely monitor patients with a history of increased IOP or open angle glaucoma (5.9).
- Motor and Verbal Tics, and Worsening of Tourette’s Syndrome: Before initiating Focalin, assess the family history and clinically evaluate patients for tics or Tourette’s syndrome. Regularly monitor patients for the emergence or worsening of tics or Tourette’s syndrome. Discontinue treatment if clinically appropriate (5.10).

6 ADVERSE REACTIONS

The most common adverse reactions (greater than or equal to 5% and twice the rate of placebo) in pediatric patients 6 to 17 years were abdominal pain, fever, nausea, and anorexia (6.1).

To report SUSPECTED ADVERSE REACTIONS, contact Sandoz Inc. at 1-800-525-8747 or FDA at 1-800-FDA-1088 or www.fda.gov/medwatch.

7 DRUG INTERACTIONS

- Antihypertensive Drugs: Monitor blood pressure. Adjust dosage of antihypertensive drug as needed (7.1).

FULL PRESCRIBING INFORMATION

WARNING: ABUSE, MISUSE, AND ADDICTION

Focalin has a high potential for abuse and misuse, which can lead to the development of a substance use disorder, including addiction. Misuse and abuse of CNS stimulants, including Focalin, can result in overdose and death [see Overdosage (10)], and this risk is increased with higher doses or unapproved methods of administration, such as snorting or injection.

Before prescribing Focalin, assess each patient’s risk for abuse, misuse, and addiction. Educate patients and their families about these risks, proper storage of the drug, and proper disposal of any unused drug. Throughout Focalin treatment, reassess each patient’s risk of abuse, misuse, and addiction and frequently monitor for signs and symptoms of abuse, misuse, and addiction [see Warnings and Precautions (5.1) and Drug Abuse and Dependence (9.2)].

1 INDICATIONS AND USAGE

Focalin is indicated for the treatment of Attention Deficit Hyperactivity Disorder (ADHD) [see Clinical Studies (14)].

2 DOSAGE AND ADMINISTRATION

2.1 Pretreatment Screening

Prior to treating patients with Focalin, assess:

- for the presence of cardiac disease (i.e., perform a careful history, family history of sudden death or ventricular arrhythmia, and physical exam) [see Warnings and Precautions (5.2)].
- the family history and clinically evaluate patients for motor or verbal tics or Tourette’s syndrome before initiating Focalin [see Warnings and Precautions (5.10)].

2.2 Recommended Dosage

Patients New to Methylphenidate

The recommended starting dose of Focalin for pediatric patients who are not currently taking racemic methylphenidate, or for patients who are on stimulants other than methylphenidate, is 5 mg daily (2.5 mg twice daily) with or without food.

Patients Currently on Methylphenidate

The recommended starting dose of Focalin for pediatric patients currently using methylphenidate is half (1/2) the total daily dose of racemic methylphenidate.

Titration Schedule

The dose may be titrated weekly in increments of 2.5 mg to 5 mg to a maximum of 20 mg daily (10 mg twice daily). The dose should be individualized according to the needs and response of the patient.

2.3 Administration Instructions

Focalin is administered orally twice daily, at least 4 hours apart.

2.4 Dosage Reduction and Discontinuation

If paradoxical aggravation of symptoms or other adverse reactions occur, reduce the dosage, or if necessary, discontinue Focalin. If improvement is not observed after appropriate dosage adjustment over a one-month period, the drug should be discontinued.

3 DOSAGE FORMS AND STRENGTHS

Focalin (dexmethylphenidate hydrochloride) tablets are D-shaped, embossed “D” on upper convex face and dosage strength on lower convex face in the following colors:

- 2.5 mg tablets – blue
- 5 mg tablets – yellow
- 10 mg tablets – white

4 CONTRAINDICATIONS

- Hypersensitivity to methylphenidate or other components of Focalin. Hypersensitivity reactions, such as angioedema and anaphylactic reactions have been reported in patients treated with methylphenidate [see Adverse Reactions (6.1)].
- Concomitant treatment with monoamine oxidase inhibitors (MAOIs), or within 14 days following discontinuation of treatment with an MAOI, because of the risk of hypertensive crises [see Drug Interactions (7.1)].

5 WARNINGS AND PRECAUTIONS

5.1 Abuse, Misuse, and Addiction

Focalin has a high potential for abuse and misuse. The use of Focalin exposes individuals to the risks of abuse and misuse, which can lead to the development of a substance use disorder, including addiction. Focalin can be diverted for non-medical use into illicit channels or distribution [see Drug Abuse and Dependence (9.2)]. Misuse and abuse of CNS stimulants, including Focalin, can result in overdose and death [see Overdosage (10)], and this risk is increased with higher doses or unapproved methods of administration, such as snorting or injection.

Before prescribing Focalin, assess each patient’s risk for abuse, misuse, and addiction. Educate patients and their families about these risks and proper disposal of any unused drug. Advise patients to store Focalin in a safe place, preferably locked, and instruct patients to not give Focalin to anyone else. Throughout Focalin treatment, reassess each patient’s risk of abuse, misuse, and addiction and frequently monitor for signs and symptoms of abuse, misuse, and addiction.

5.2 Risks to Patients with Serious Cardiac Disease

Sudden death has been reported in patients with structural cardiac abnormalities or other serious cardiac disease who were treated with CNS stimulants at the recommended ADHD dosage.

Avoid Focalin use in patients with known structural cardiac abnormalities, cardiomyopathy, serious cardiac arrhythmia, coronary artery disease, or other serious cardiac disease.

5.3 Increased Blood Pressure and Heart Rate

CNS stimulants cause an increase in blood pressure (mean increase approximately 2 to 4 mmHg) and heart rate (mean increase approximately 3 to 6 beats per minute). Some patients may have larger increases. Monitor all Focalin-treated patients for hypertension and tachycardia.

5.4 Psychiatric Adverse Reactions

Exacerbation of Preexisting Psychosis

CNS stimulants may exacerbate symptoms of behavior disturbance and thought disorder in patients with a preexisting psychotic disorder.

Induction of a Manic Episode in Patients with Bipolar Disorder

CNS stimulants may induce a manic or mixed mood episode in patients. Prior to initiating Focalin treatment, screen patients for risk factors for developing a manic episode (e.g., comorbid or history of depressive symptoms or a family history of suicide, bipolar disorder, or depression).

New Psychotic or Manic Symptoms

CNS stimulants, at the recommended dosage, may cause psychotic or manic symptoms (e.g., hallucinations, delusional thinking, or mania) in patients without a prior history of psychotic illness or mania. In a pooled analysis of multiple short-term, placebo-controlled studies of CNS stimulants, psychotic, or manic symptoms occurred in approximately 0.1% of CNS stimulant-treated patients, compared to 0% of placebo-treated patients. If such symptoms occur, consider discontinuing Focalin.

5.5 Priapism

Prolonged and painful erections, sometimes requiring surgical intervention, have been reported with methylphenidate use in both adult and pediatric male patients. Although priapism was not reported with methylphenidate initiation, it developed after some time on methylphenidate, often subsequent to an increase in dosage. Priapism also occurred during methylphenidate withdrawal (drug holidays or during discontinuation).

Focalin-treated patients who develop abnormally sustained or frequent and painful erections should seek immediate medical attention.

5.6 Peripheral Vasculopathy, Including Raynaud’s Phenomenon

CNS stimulants, including Focalin, used to treat ADHD are associated with peripheral vasculopathy, including Raynaud’s phenomenon. Signs and symptoms are usually intermittent and mild; however, sequelae have included digital ulceration and/or soft tissue breakdown. Effects of peripheral vasculopathy, including Raynaud’s phenomenon, were observed in post-marketing reports and at the therapeutic dosages of CNS stimulants in all age groups throughout the course of treatment. Signs and symptoms generally improved after dosage reduction or discontinuation of the CNS stimulant.

Careful observation for digital changes is necessary during Focalin treatment. Further clinical evaluation (e.g., rheumatology referral) may be appropriate for Focalin-treated patients who develop signs or symptoms of peripheral vasculopathy.

5.7 Long-Term Suppression of Growth in Pediatric Patients

CNS stimulants have been associated with weight loss and slowing of growth rate in pediatric patients.

Careful follow-up of weight and height in patients ages 7 to 10 years who were randomized to either methylphenidate or non-medication treatment groups over 14 months, as well as in naturalistic subgroups of newly methylphenidate-treated and non-medication treated patients over 36 months (to the ages of 10 to 13 years), suggests that pediatric patients who received methylphenidate for 7 days per week throughout the year had a temporary slowing in growth rate (on average, a total of about 2 cm less growth in height and 2.7 kg less growth in weight over 3 years), without evidence of growth rebound during this development period.

Closely monitor growth (weight and height) in Focalin-treated pediatric patients. Pediatric patients who are not growing or gaining height or weight as expected may need to have their treatment interrupted.

5.8 Acute Angle Closure Glaucoma

There have been reports of angle closure glaucoma associated with methylphenidate treatment.

Although the mechanism is not clear, Focalin-treated patients considered at risk for acute angle closure glaucoma (e.g.,

patients with significant hyperopia) should be evaluated by an ophthalmologist.

5.9 Increased Intraocular Pressure and Glaucoma

There have been reports of an elevation of intraocular pressure (IOP) associated with methylphenidate treatment [see Adverse Reactions (6.2)].

Prescribe Focalin to patients with open-angle glaucoma or abnormally increased IOP only if the benefit of treatment is considered to outweigh the risk. Closely monitor Focalin-treated patients with a history of abnormally increased IOP or open angle glaucoma.

5.10 Motor and Verbal Tics, and Worsening of Tourette’s Syndrome

CNS stimulants, including methylphenidate, have been associated with the onset or exacerbation of motor and verbal tics.

Worsening of Tourette’s syndrome has also been reported [see Adverse Reactions (6.2)].

Before initiating Focalin, assess the family history and clinically evaluate patients for tics or Tourette’s syndrome. Regularly monitor Focalin-treated patients for the emergence or worsening of tics or Tourette’s syndrome, and discontinue treatment if clinically appropriate.

6 ADVERSE REACTIONS

The following are discussed in more detail in other sections of the labeling:

- Abuse, Misuse, and Addiction [see Boxed Warning, Warnings and Precautions (5.1), Drug Abuse and Dependence (9.2, 9.3)]
- Known hypersensitivity to methylphenidate or other ingredients of Focalin [see Contraindications (4)]
- Hypertensive crisis with Concomitant Use of Monoamine Oxidase Inhibitors [see Contraindications (4), Drug Interactions (7.1)]
- Risks to Patients with Serious Cardiac Disease [see Warnings and Precautions (5.2)]
- Increased Blood Pressure and Heart Rate [see Warnings and Precautions (5.3)]
- Psychiatric Adverse Reactions [see Warnings and Precautions (5.4)]
- Priapism [see Warnings and Precautions (5.5)]
- Peripheral Vasculopathy, Including Raynaud’s phenomenon [see Warnings and Precautions (5.6)]
- Long-Term Suppression of Growth in Pediatric Patients [see Warnings and Precautions (5.7)]
- Acute Angle Closure Glaucoma [see Warnings and Precautions (5.8)]
- Increased Intraocular Pressure and Glaucoma [see Warnings and Precautions (5.9)]
- Motor and Verbal Tics, and Worsening of Tourette’s Syndrome [see Warnings and Precautions (5.10)]

6.1 Clinical Trials Experience

Because clinical trials are conducted under widely varying conditions, adverse reaction rates observed in the clinical trials of a drug cannot be directly compared to rates in the clinical trials of another drug and may not reflect the rates observed in clinical practice.

Adverse Reactions in Studies with Focalin in Pediatric Patients with ADHD

The safety data in this section is based on data related to Focalin exposure during the premarketing development program in a total of 696 participants in clinical trials (684 patients, 12 healthy adult subjects). These participants received Focalin 5, 10, or 20 mg/day. The 684 ADHD patients (ages 6 to 17 years) were evaluated in 2 controlled clinical studies, 2 clinical pharmacology studies, and 2 open-label long-term safety studies.

Most Common Adverse Reactions (incidence of greater than or equal to 5% and at least twice placebo): abdominal pain, fever, anorexia, and nausea

Adverse Reactions Leading to Discontinuation: Overall, 50 of 684 (7.3%) pediatric patients treated with Focalin experienced an adverse reaction that resulted in discontinuation. The most common reasons for discontinuation were twitching (described as motor or vocal tics), anorexia, insomnia, and tachycardia (approximately 1% each).

Table 1 enumerates adverse reactions for two, placebo-controlled, parallel group studies in pediatric patients with ADHD taking Focalin doses of 5, 10, and 20 mg/day. The table includes only those reactions that occurred in patients treated with Focalin for which the incidence was at least 5% and twice the incidence among placebo-treated patients.

Table 1: Common Adverse Reactions in Pediatric Patients (6 to 17 years of age) With ADHD
System organ class | Adverse reactions | Focalin (N = 79) | Placebo (N = 82)
Body as a whole | Abdominal pain | 15% | 6%
 | Fever | 5% | 1%
Digestive system | Anorexia | 6% | 1%
 | Nausea | 9% | 1%
Abbreviation: ADHD, attention deficit hyperactivity disorder.

6.2 Postmarketing Experience

The following additional adverse reactions have been identified during postapproval use of dexmethylphenidate. Because these reactions are reported voluntarily from a population of uncertain size, it is not always possible to reliably estimate their frequency or establish a causal relationship to drug exposure.

Musculoskeletal: rhabdomyolysis

Immune System Disorders: hypersensitivity reactions, such as angioedema, anaphylactic reactions

Adverse Reactions Reported with All Ritalin and Focalin Formulations

The following adverse reactions associated with the use of all Ritalin and Focalin formulations were identified in clinical trials, spontaneous reports, and literature. Because these reactions were reported voluntarily from a population of uncertain size, it is not always possible to estimate their frequency reliably or to establish a causal relationship to drug exposure.

Infections and Infestations: nasopharyngitis

Blood and the Lymphatic System Disorders: leukopenia, thrombocytopenia, anemia

Immune System Disorders: hypersensitivity reactions, including angioedema and anaphylaxis

Metabolism and Nutrition Disorders: decreased appetite, reduced weight gain, and suppression of growth during prolonged use in pediatric patients

Psychiatric Disorders: insomnia, anxiety, restlessness, agitation, psychosis (sometimes with visual and tactile hallucinations), depressed mood, depression

Nervous System Disorders: headache, dizziness, tremor, dyskinesia, including choreoatheetoid movements, drowsiness, convulsions, cerebrovascular disorders (including vasculitis, cerebral hemorrhages, and cerebrovascular accidents), serotonin syndrome in combination with serotonergic drugs

Eye Disorders: blurred vision, difficulties in visual accommodation

Cardiac Disorders: tachycardia, palpitations, increased blood pressure, arrhythmias, angina pectoris

Respiratory, Thoracic, and Mediastinal Disorders: cough

Gastrointestinal Disorders: dry mouth, nausea, vomiting, abdominal pain, dyspepsia

Hepatobiliary Disorders: abnormal liver function, ranging from transaminase elevation to severe hepatic injury

Skin and Subcutaneous Tissue Disorders: hyperhidrosis, pruritus, urticaria, exfoliative dermatitis, scalp hair loss, erythema multiforme rash, thrombocytopenic purpura

Musculoskeletal and Connective Tissue Disorders: arthralgia, muscle cramps, rhabdomyolysis, trismus

Investigations: weight loss (adult ADHD patients)

Vascular Disorders: peripheral coldness, Raynaud's phenomenon

Additional Adverse Reactions Reported with Other Methylphenidate-Containing Products

The list below shows adverse reactions not listed with Ritalin and Focalin formulations that have been reported with other methylphenidate products based on clinical trials data and post-marketing spontaneous reports.

Blood and Lymphatic Disorders: pancytopenia

Immune System Disorders: hypersensitivity reactions, such as auricular swelling

Psychiatric Disorders: affect lability, mania, disorientation, libido changes

Nervous System Disorders: migraine, motor and verbal tics

Eye Disorders: diplopia, increased intraocular pressure, mydriasis

Cardiac Disorders: sudden cardiac death, myocardial infarction, bradycardia, extrasystole, supraventricular tachycardia, ventricular extrasystole

Respiratory, Thoracic, and Mediastinal Disorders: pharyngolaryngeal pain, dyspnea

Gastrointestinal Disorders: diarrhea, constipation

Skin and Subcutaneous Tissue Disorders: angioneurotic edema, erythema, fixed drug eruption

Musculoskeletal, Connective Tissue, and Bone Disorders: myalgia, muscle twitching

Renal and Urinary Disorders: hematuria

Reproductive System and Breast Disorders: gynecomastia

General Disorders: fatigue

Urogenital Disorders: priapism

7 DRUG INTERACTIONS

7.1 Clinically Important Drug Interactions with Focalin

Table 2 presents clinically important drug interactions with Focalin.

Table 2: Clinically Important Drug Interactions with Focalin
Monoamine Oxidase Inhibitors (MAOIs)
Clinical impact | Concomitant use of MAOIs and CNS stimulants, including Focalin, can cause hypertensive crisis. Potential outcomes include death, stroke, myocardial infarction, aortic dissection, ophthalmological complications, eclampsia, pulmonary edema, and renal failure [see Contraindications (4)].
Intervention | Concomitant use of Focalin with MAOIs or within 14 days after discontinuing MAOI treatment is contraindicated.
Antihypertensive Drugs
Clinical impact | Focalin may decrease the effectiveness of drugs used to treat hypertension [see Warnings and Precautions (5.3)].
Intervention | Adjust the dosage of the antihypertensive drug as needed.
Halogenated Anesthetics
Clinical impact | Concomitant use of halogenated anesthetics and Focalin may increase the risk of sudden blood pressure and heart rate increase during surgery.
Intervention | Monitor blood pressure and avoid use of Focalin in patients being treated with anesthetics on the day of surgery.
Risperidone
Clinical impact | Combined use of methylphenidate with risperidone when there is a change, whether an increase or decrease, in dosage of either or both medications, may increase the risk of extrapyramidal symptoms (EPS).
Intervention | Monitor for signs of EPS.

8 USE IN SPECIFIC POPULATIONS

8.1 Pregnancy

Pregnancy Exposure Registry

There is a pregnancy exposure registry that monitors pregnancy outcomes in women exposed to ADHD medications, including Focalin, during pregnancy. Healthcare providers are encouraged to register patients by calling the National Pregnancy Registry for ADHD medications at 1-866-961-2388 or visiting https://womensmentalhealth.org/adhd-medications/.

Risk Summary

Dexmethylphenidate is the d-threo enantiomer of racemic methylphenidate. Published studies and postmarketing reports on methylphenidate use during pregnancy have not identified a drug-associated risk of major birth defects, miscarriage or adverse maternal or fetal outcomes. There may be risks to the fetus associated with the use of CNS stimulants during pregnancy (see Clinical Considerations). Embryo-fetal development studies in rats showed delayed fetal skeletal ossification at doses up to 5 times the maximum recommended human dose (MRHD) of 20 mg/day given to adults based on plasma levels. A decrease in pup weight in males was observed in a pre- and post-natal development study with oral administration of methylphenidate to rats throughout pregnancy and lactation at doses 5 times the MRHD of 20 mg/day given to adults based on plasma levels. Plasma levels in adults were comparatively similar to plasma levels in adolescents (see Data).

The estimated background risk of major birth defects and miscarriage for the indicated population is unknown. All pregnancies have a background risk of birth defect, loss, or other adverse outcomes. In the U.S. general population, the estimated background risk of major birth defects and miscarriage in clinically recognized pregnancies is 2% to 4% and 15% to 20%, respectively.

Clinical Considerations

Fetal/Neonatal Adverse Reactions

CNS stimulants, such as Focalin, can cause vasoconstriction and thereby decrease placental perfusion. No fetal and/or neonatal adverse reactions have been reported with the use of therapeutic doses of methylphenidate during pregnancy; however, premature delivery and low birth weight infants have been reported in amphetamine-dependent mothers.

Data

Animal Data

In embryo-fetal development studies conducted in rats and rabbits, dexmethylphenidate was administered orally at doses of up to 20 and 100 mg/kg/day, respectively, during the period of organogenesis. No evidence of malformations was found in either the rat or rabbit study; however, delayed fetal skeletal ossification was observed at the highest dose level in rats. When dexmethylphenidate was administered to rats throughout pregnancy and lactation at doses of up to 20 mg/kg/day, post-weaning body weight gain was decreased in male offspring at the highest dose, but no other effects on postnatal development were observed. At the highest doses tested, plasma levels [area under the curves (AUCs)] of dexmethylphenidate in pregnant rats and rabbits were approximately 5 and 1 times, respectively, those in adults dosed with the MRHD of 20 mg/day.

Racemic methylphenidate has been shown to cause malformations (increased incidence of fetal spina bifida) in rabbits when given in doses of 200 mg/kg/day throughout organogenesis.

8.2 Lactation

Risk Summary

Dexmethylphenidate is the d-threo enantiomer of racemic methylphenidate. Limited published literature, based on milk sampling from seven mothers reports that methylphenidate is present in human milk, which resulted in infant doses of 0.16% to 0.7% of the maternal weight-adjusted dosage and a milk/plasma ratio ranging between 1.1 and 2.7. There are no reports of adverse effects on the breastfed infant and no effects on milk production. Long-term neurodevelopmental effects on infants from stimulant exposure are unknown. The developmental and health benefits of breastfeeding should be considered along with the mother’s clinical need for Focalin and any potential adverse effects on the breastfed infant from Focalin or from the underlying maternal condition.

Clinical Considerations

Monitor breastfeeding infants for adverse reactions, such as agitation, insomnia, anorexia, and reduced weight gain.

8.4 Pediatric Use

The safety and effectiveness of Focalin have been established in pediatric patients aged 6 to 17 years in two adequate and well-controlled clinical trials [see Clinical Studies (14)].

The safety and effectiveness of Focalin in pediatric patients aged less than 6 years have not been established.

The long-term efficacy of Focalin in pediatric patients has not been established.

Long-Term Suppression of Growth

Growth should be monitored during treatment with stimulants, including Focalin. Pediatric patients who are not growing or gaining weight as expected may need to have their treatment interrupted [see Warnings and Precautions (5.7)].

Juvenile Animal Toxicity Data

Rats treated with racemic methylphenidate early in the postnatal period through sexual maturation demonstrated a decrease in spontaneous locomotor activity in adulthood. A deficit in acquisition of a specific learning task was observed in females only. The doses at which these findings were observed are at least 6 times the MRHD of 60 mg/day given to children on a mg/m^2 basis.

In a study conducted in young rats, racemic methylphenidate was administered orally at doses of up to 100 mg/kg/day for 9 weeks, starting early in the postnatal period (postnatal Day 7) and continuing through sexual maturity (postnatal week 10). When these animals were tested as adults (postnatal Weeks 13 to 14), decreased spontaneous locomotor activity was observed in males and females previously treated with 50 mg/kg/day (approximately 4 times the MRHD of 60 mg of racemic methylphenidate given to children on a mg/m^2 basis) or greater, and a deficit in the acquisition of a specific learning task was seen in females exposed to the highest dose (8 times the MRHD given to children on a mg/m^2 basis). The no effect level for juvenile neurobehavioral development in rats was 5 mg/kg/day (approximately 0.5 times the MRHD given to children on a mg/m^2 basis). The clinical significance of the long-term behavioral effects observed in rats is unknown.

8.5 Geriatric Use

Focalin has not been studied in the geriatric population.

9 DRUG ABUSE AND DEPENDENCE

9.1 Controlled Substance

Focalin contains dexmethylphenidate hydrochloride, a Schedule II controlled substance.

9.2 Abuse

Focalin has a high potential for abuse and misuse which can lead to the development of a substance use disorder, including addiction [see Warnings and Precautions (5.1)]. Focalin can be diverted for non-medical use into illicit channels or distribution.

Abuse is the intentional non-therapeutic use of a drug, even once, to achieve a desired psychological or physiological effect. Misuse is the intentional use, for therapeutic purposes, of a drug by an individual in a way other than prescribed by a health care provider or for whom it was not prescribed. Drug addiction is a cluster of behavioral, cognitive, and physiological phenomena that may include a strong desire to take the drug, difficulties in controlling drug use (e.g., continuing drug use despite harmful consequences, giving a higher priority to drug use than other activities and obligations), and possible tolerance or physical dependence.

Misuse and abuse of methylphenidate may cause increased heart rate, respiratory rate, or blood pressure; sweating; dilated pupils; hyperactivity; restlessness; insomnia; decreased appetite; loss of coordination; tremors; flushed skin; vomiting; and/or abdominal pain. Anxiety, psychosis, hostility, aggression, and suicidal or homicidal ideation have also been observed with CNS stimulants abuse and/or misuse. Misuse and abuse of CNS stimulants, including Focalin, can result in overdose and death [see Overdosage (10)], and this risk is increased with higher doses or unapproved methods of administration, such as snorting or injection.

9.3 Dependence

Physical Dependence

Focalin may produce physical dependence. Physical dependence is a state that develops as a result of physiological adaptation in response to repeated drug use, manifested by withdrawal signs and symptoms after abrupt discontinuation or a significant dose reduction of a drug.

Withdrawal signs and symptoms after abrupt discontinuation or dose reduction following prolonged use of CNS stimulants including Focalin include dysphoric mood; depression; fatigue; vivid, unpleasant dreams; insomnia or hypersomnia; increased appetite; and psychomotor retardation or agitation.

Tolerance

Focalin may produce tolerance. Tolerance is a physiological state characterized by a reduced response to a drug after repeated administration (i.e., a higher dose of a drug is required to produce the same effect that was once obtained at a lower dose).

10 OVERDOSAGE

Clinical Effects of Overdose

Overdose of CNS stimulants is characterized by the following sympathomimetic effects:

- Cardiovascular effects including tachyarrhythmias, and hypertension or hypotension. Vasospasm, myocardial infarction, or aortic dissection may precipitate sudden cardiac death. Takotsubo cardiomyopathy may develop.
- CNS effects including psychomotor agitation, confusion, and hallucinations. Serotonin syndrome, seizures, cerebral vascular accidents, and coma may occur.
- Life-threatening hyperthermia (temperatures greater than 104°F) and rhabdomyolysis may develop.

Overdose Management

Consider the possibility of multiple drug ingestion. Because methylphenidate has a large volume of distribution and is rapidly metabolized, dialysis is not useful. Consider contacting the Poison Help line (1-800-222-1222) or a medical toxicologist for additional overdose management recommendations.

11 DESCRIPTION

Focalin contains dexmethylphenidate hydrochloride, a CNS stimulant. Dexmethylphenidate hydrochloride is the d-threo enantiomer of racemic methylphenidate hydrochloride. Focalin is available as 2.5 mg, 5 mg, and 10 mg strength tablets for oral administration.

Chemically, dexmethylphenidate hydrochloride is methyl α-phenyl-2-piperidineacetate hydrochloride, (R,R’)-(+)-. Its molecular formula is C14H19NO2•HCl. Its structural formula is:

Note: * = asymmetric carbon centers

Dexmethylphenidate hydrochloride is a white to off-white powder. Its solutions are acid to litmus. It is freely soluble in water and in methanol, soluble in alcohol, and slightly soluble in chloroform and in acetone. Its molecular weight is 269.77 g/mol.

Inactive ingredients: FD&C blue no.1 #5516 aluminum lake (2.5 mg tablets), D&C yellow #10 aluminum lake (5 mg tablets), the 10 mg tablet contains no dye; lactose monohydrate, magnesium stearate, microcrystalline cellulose, pregelatinized starch and sodium starch glycolate.

12 CLINICAL PHARMACOLOGY

12.1 Mechanism of Action

Dexmethylphenidate hydrochloride is a CNS stimulant. The mode of therapeutic action in ADHD is not known.

12.2 Pharmacodynamics

Pharmacodynamics

Dexmethylphenidate is the more pharmacologically active d-enantiomer of racemic methylphenidate. Methylphenidate blocks the reuptake of norepinephrine and dopamine into the presynaptic neuron and increase the release of these monoamines into the extraneuronal space.

Cardiac Electrophysiology

A formal QT study has not been conducted in patients taking Focalin; however, a large QT effect is not expected. At the recommended maximum total daily dosage of 40 mg, Focalin XR (dexmethylphenidate) extended-release capsule does not prolong the QTc interval to any clinically relevant extent.

12.3 Pharmacokinetics

Absorption

Dexmethylphenidate hydrochloride is readily absorbed following oral administration of Focalin. In patients with ADHD, plasma dexmethylphenidate concentrations increase rapidly, reaching a maximum in the fasted state at about 1 to 1.5 hours postdose. No differences in the pharmacokinetics of Focalin were noted following single and repeated twice daily dosing, thus indicating no significant drug accumulation in children with ADHD.

After single dose administration of Focalin to pediatric patients, dexmethylphenidate exposure (Cmax and AUC0-inf) showed dose-proportional increase in the range of 2.5 mg to 10 mg. Comparable plasma dexmethylphenidate levels were achieved following single dl-threo-methylphenidate HCl doses given as capsules in twice the total mg amount (equimolar with respect to Focalin).

Approximately 90% of the dose is absorbed after oral administration of radiolabeled racemic methylphenidate. However, due to first pass metabolism the mean absolute bioavailability of dexmethylphenidate when administered in various formulations was 22% to 25%.

Effect of Food

High fat breakfast did not significantly affect Cmax or AUC0-inf of dexmethylphenidate when two 10 mg Focalin tablets were administered, but delayed Tmax from 1.5 hours post dose to 2.9 hours post dose.

Distribution

The plasma protein binding of dexmethylphenidate is not known; racemic methylphenidate is bound to plasma proteins by 12% to 15%, independent of concentration. Dexmethylphenidate shows a volume of distribution of 2.65 ± 1.11 L/kg.

Elimination

Plasma dexmethylphenidate concentrations declined exponentially following oral administration of Focalin. Intravenous dexmethylphenidate was eliminated with a mean clearance of 0.40 ± 0.12 L/hr/kg. The mean terminal elimination half-life of dexmethylphenidate was approximately 2.2 hours.

Metabolism

In humans, dexmethylphenidate is metabolized primarily via de-esterification to d-α-phenyl-piperidine acetic acid (also known as d-ritalinic acid). This metabolite has little or no pharmacological activity. There is little or no in vivo interconversion to the l-threo-enantiomer.

Excretion

After oral dosing of radiolabeled racemic methylphenidate in humans, about 90% of the radioactivity was recovered in urine. The main urinary metabolite of racemic dl-methylphenidate was dl-ritalinic acid, accountable for approximately 80% of the dose. Urinary excretion of parent compound accounted for 0.5% of an intravenous dose.

Studies in Special Populations

Male and Female Patients

Pharmacokinetic parameters were similar for boys and girls (mean age 10 years).

In a single dose study conducted in adults, the mean dexmethylphenidate AUC0-inf values (adjusted for body weight) following single two 10 mg doses of Focalin were 25% to 35% higher in adult female volunteers (n = 6) compared to male volunteers (n = 9). Both Tmax and t1/2 were comparable for males and females.

Racial or Ethnic Groups

There is insufficient experience with the use of Focalin to detect ethnic variations in pharmacokinetics.

Pediatric Patients

The pharmacokinetics of dexmethylphenidate after Focalin administration have not been studied in children less than 6 years of age. When single doses of Focalin were given to children between the ages of 6 to 12 years and healthy adult volunteers, Cmax of dexmethylphenidate was similar, however, pediatric patients showed somewhat lower AUCs compared to the adults.

Patients with Renal Impairment

There is no experience with the use of Focalin in patients with renal impairment. Since renal clearance is not an important route of methylphenidate clearance, renal impairment is expected to have little effect on the pharmacokinetics of Focalin.

Patients with Hepatic Impairment

There is no experience with the use of Focalin in patients with hepatic impairment.

Drug Interaction Studies

Methylphenidate is not metabolized by cytochrome P450 (CYP) isoenzymes to a clinically relevant extent. Inducers or inhibitors of CYPs are not expected to have any relevant impact on methylphenidate pharmacokinetics. Conversely, the d- and l-enantiomers of methylphenidate did not relevantly inhibit CYP1A2, 2C8, 2C9, 2C19, 2D6, 2E1, or 3A. Clinically, methylphenidate coadministration did not increase plasma concentrations of the CYP2D6 substrate desipramine.

13 NONCLINICAL TOXICOLOGY

13.1 Carcinogenesis, Mutagenesis, and Impairment of Fertility

Carcinogenesis

Lifetime carcinogenicity studies have not been carried out with dexmethylphenidate. In a lifetime carcinogenicity study carried out in B6C3F1 mice, racemic methylphenidate caused an increase in hepatocellular adenomas, and in males only, an increase in hepatoblastomas was seen at a daily dose of approximately 60 mg/kg/day. This dose is approximately 2 times the MRHD of 60 mg/day of racemic methylphenidate given to children on a mg/m^2 basis. Hepatoblastoma is a relatively rare rodent malignant tumor type. There was no increase in total malignant hepatic tumors. The mouse strain used is sensitive to the development of hepatic tumors and the significance of these results to humans is unknown. Racemic methylphenidate did not cause any increase in tumors in a lifetime carcinogenicity study carried out in F344 rats; the highest dose used was approximately 45 mg/kg/day, which is approximately 4 times the MRHD (children) of 60 mg/day of racemic methylphenidate on a mg/m^2 basis.

In a 24-week carcinogenicity study with racemic methylphenidate in the transgenic mouse strain p53+/-, which is sensitive to genotoxic carcinogens, there was no evidence of carcinogenicity. Male and female mice were fed diets containing the same concentrations as in the lifetime carcinogenicity study; the high-dose group was exposed to 60-74 mg/kg/day of racemic methylphenidate.

Mutagenesis

Dexmethylphenidate was not mutagenic in the in vitro Ames reverse mutation assay, in the in vitro mouse lymphoma cell forward mutation assay, or in the in vivo mouse bone marrow micronucleus test. In an in vitro assay using cultured Chinese Hamster Ovary cells treated with racemic methylphenidate, sister chromatid exchanges and chromosome aberrations were increased, indicative of a weak clastogenic response.

Impairment of Fertility

No human data on the effect of methylphenidate on fertility are available.

Fertility studies have not been conducted with dexmethylphenidate. Racemic methylphenidate did not impair fertility in male or female mice that were fed diets containing the drug in an 18-week continuous breeding study. The study was conducted at doses of up to 160 mg/kg/day, approximately 10 times the MRHD of 60 mg/day of racemic methylphenidate given adolescents on a mg/m^2 basis.

14 CLINICAL STUDIES

The efficacy of Focalin for the treatment of ADHD was established in two double-blind, parallel-group, placebo-controlled trials in untreated or previously treated patients (ages 6 to 17 years old) who met The Diagnostic and Statistical Manual of Mental Disorders, Fourth Edition (DSM-IV) criteria for ADHD inattentive, hyperactive-impulsive, or combined inattentive/hyperactive-impulsive subtypes. The sample was predominantly younger (ages 6 to 12 years); thus, the findings are most pertinent to this age group.

In Study 1, patients were randomized to receive either Focalin (5, 10, or 20 mg/day total dose), racemic methylphenidate HCl (10, 20, or 40 mg/day total dose), or placebo in a multicenter, 4-week, parallel group study in 132 pediatric patients. Patients received study medication twice daily separated by a 3.5 to 5.5 hours interval. Treatment was initiated with the lowest dose, and doses could be doubled at weekly intervals, depending on clinical response and tolerability, up to the maximum dose. The primary outcome was change from baseline to week 4 of the average score (an average of 2 ratings during the week) of the teacher’s version of the Swanson, Nolan and Pelham (SNAP)-ADHD Rating Scale. This 18 item scale measures ADHD symptoms of inattention and hyperactivity/impulsivity, rated on a scale of 0 (Not at All) to 3 (Very Much). Patients treated with Focalin showed a statistically significant improvement in symptom scores from baseline over patients who received placebo (Table 3).

Table 3: Summary of Efficacy Results from ADHD Acute-Phase Study in Pediatric Patients (6 – 17 years) (Study 1)
Study number | Treatment group | Primary efficacy measure: teacher SNAP-ADHD total Scorea
 |  | Mean baseline score (SD) | Mean change from baseline Week 4 score (SD)
Study 1 | Focalin 5-20 mg/dayb (n = 44) | 1.4 (0.7) (n = 42) | - 0.7 (0.7) (n = 42)
 | Placebo (n = 42) | 1.6 (0.7) (n = 41) | - 0.2 (0.7) (n = 39)
Abbreviations: ADHD, attention deficit hyperactivity disorder; SD, standard deviation; SNAP; swanson, Nolan and Pelham; n, number of patients available at the assessment time point.
aAverage of two ratings.
bStatistically significantly different from placebo.

Study 2 was a multicenter, placebo-controlled, double-blind, 2-week treatment withdrawal study in 75 children (ages 6 to 12 years) who were responders during a 6-week, open-label initial treatment period. Children took study medication twice a day separated by a 3.5 to 5.5 hour interval. The primary outcome was proportion of treatment failures at the end of the 2-week withdrawal phase, where treatment failure was defined as a rating of 6 (much worse) or 7 (very much worse) on the Investigator Clinical Global Impression - Improvement (CGI-I). Patients continued on Focalin showed a statistically significant lower rate of failure over patients who received placebo (Table 4).

Table 4: Summary of Efficacy Results from ADHD Randomized Withdrawal Study in Pediatric Patients (6 – 17 years) (Study 2)
Study number | Treatment group | Primary efficacy measure: proportion of treatment failurea
 |  | Number of treatment failures / Number of randomized patients | Percentage
Study 2 | Focalin 5-20 mg/dayb | 6/35 | 17.1%
 | Placebo | 25/40 | 62.5%
Abbreviation: ADHD, attention deficit hyperactivity disorder.
aOne patient did not have the value at Visit 10 and hence not included in this analysis.
bStatistically significantly different from placebo.

16 HOW SUPPLIED/STORAGE AND HANDLING

Focalin (dexmethylphenidate hydrochloride) tablets (D-shaped, embossed “D” on upper convex face and dosage strength on lower convex face) are available as follows:

- 2.5 mg tablets (NDC 66758-250-01) blue, supplied in bottles of 100
- 5 mg tablets (NDC 66758-251-01) yellow, supplied in bottles of 100
- 10 mg tablets (NDC 66758-252-01) white, supplied in bottles of 100

Store at 20°C to 25°C (68°F to 77°F); excursions permitted between 15°C and 30°C (59°F and 86°F) [see USP Controlled Room Temperature].

Protect from light and moisture. Dispense in tight, light-resistant container (USP).

17 PATIENT COUNSELING INFORMATION

Advise the patient to read the FDA-approved patient labeling (Medication Guide).

Abuse, Misuse, and Addiction

Educate patients and their families about the risks of abuse, misuse, and addiction of Focalin, which can lead to overdose and death, and proper disposal of any unused drug [see Warnings and Precautions (5.1), Drug Abuse and Dependence (9.2), Overdosage (10)]. Advise patients to store Focalin in a safe place, preferably locked, and instruct patients to not give Focalin to anyone else.

Risks to Patients with Serious Cardiac Disease

Advise patients that there are potential risks to patients with serious cardiac disease, including sudden death, with Focalin use. Instruct patients to contact a healthcare provider immediately if they develop symptoms, such as exertional chest pain, unexplained syncope, or other symptoms suggestive of cardiac disease [see Warnings and Precautions (5.2)].

Increased Blood Pressure and Heart Rate

Instruct patients that Focalin can cause elevations of their blood pressure and pulse rate [see Warnings and Precautions (5.3)].

Psychiatric Adverse Reactions

Advise patients that Focalin, at recommended doses, can cause psychotic or manic symptoms, even in patients without prior history of psychotic symptoms or mania [see Warnings and Precautions (5.4)].

Priapism

Advise patients of the possibility of painful or prolonged penile erections (priapism). Instruct them to seek immediate medical attention in the event of priapism [see Warnings and Precautions (5.5)].

Circulation Problems in Fingers and Toes [Peripheral Vasculopathy, Including Raynaud’s Phenomenon]

Instruct patients beginning treatment with Focalin about the risk of peripheral vasculopathy, including Raynaud’s phenomenon, and associated signs and symptoms: fingers or toes may feel numb, cool, painful, and/or may change color from pale, to blue, to red. Instruct patients to report to their physician any new numbness, pain, skin color change, or sensitivity to temperature in fingers or toes.

Instruct patients to call their physician immediately with any signs of unexplained wounds appearing on fingers or toes while taking Focalin. Further clinical evaluation (e.g., rheumatology referral) may be appropriate for certain patients [see Warnings and Precautions (5.6)].

Long-Term Suppression of Growth in Pediatric Patients

Advise patients that Focalin may cause slowing of growth and weight loss [see Warnings and Precautions (5.7)].

Increased Intraocular Pressure (IOP) and Glaucoma

Advise patients that IOP and glaucoma may occur during treatment with Focalin [see Warnings and Precautions (5.9)].

Motor and Verbal Tics, and Worsening of Tourette’s Syndrome

Advise patients that motor and verbal tics and worsening of Tourette’s Syndrome may occur during treatment with Focalin.

Instruct patients to notify their healthcare provider if emergence of new tics or worsening of tics or Tourette’s syndrome occurs [see Warnings and Precautions (5.10)].

Pregnancy Registry

Advise patients that there is a pregnancy exposure registry that monitors pregnancy outcomes in patients exposed to ADHD medications, including Focalin, during pregnancy [see Use in Specific Populations (8.1)].

Manufactured by
Mikart, LLC, Atlanta, GA 30318 for

Sandoz Inc., Princeton, NJ 08540

MEDICATION GUIDE
FOCALIN® (foh-kuh-lin)
(dexmethylphenidate hydrochloride)

tablets for oral use, CII

What is the most important information I should know about FOCALIN?

FOCALIN may cause serious side effects, including:

- Abuse, misuse, and addiction. FOCALIN has a high chance for abuse and misuse and may lead to substance use problems, including addiction. Misuse and abuse of FOCALIN, other methylphenidate containing medicines, and amphetamine containing medicines, can lead to overdose and death. The risk of overdose and death is increased with higher doses of FOCALIN or when it is used in ways that are not approved, such as snorting or injection.
- Your healthcare provider should check you or your child’s risk for abuse, misuse, and addiction before starting treatment with FOCALIN and will monitor you or your child during treatment.
- FOCALIN may lead to physical dependence after prolonged use, even if taken as directed by your healthcare provider.
- Do not give FOCALIN to anyone else. See “What is FOCALIN?” for more information.
- Keep FOCALIN in a safe place and properly dispose of any unused medicine. See “How should I store FOCALIN?” for more information.
- Tell your healthcare provider if you or your child have ever abused or been dependent on alcohol, prescription medicines, or street drugs.
- Risks for people with serious heart disease. Sudden death has happened in people who have heart defects or other serious heart disease.

Your healthcare provider should check you or your child carefully for heart problems before starting FOCALIN. Tell your healthcare provider if you or your child have any heart problems, heart disease, or heart defects.

Call your healthcare provider or go to the nearest hospital emergency room right away if you or your child has any signs of heart problems, such as chest pain, shortness of breath, or fainting while taking FOCALIN.

- Increased blood pressure and heart rate. Your healthcare provider should check you or your child’s blood pressure and heart rate regularly during treatment with FOCALIN.
- Mental (psychiatric) problems:
All Patients
- new or worse behavior and thought problems
- new or worse bipolar illness
- new psychotic symptoms (such as hearing voices, believing things that are not true, are suspicious) or new manic symptoms

Tell your healthcare provider about any mental problems you or your child have, or about a family history of suicide,

bipolar illness, or depression.

Call your healthcare provider right away if you or your child have any new or worsening mental symptoms or

problems while taking FOCALIN, especially seeing or hearing things that are not real, believing things that are not real, or are suspicious.

What is FOCALIN?

- FOCALIN is a central nervous system stimulant (CNS) prescription medicine. It is used for the treatment of Attention-Deficit Hyperactivity Disorder (ADHD). FOCALIN may help increase attention and decrease impulsiveness and hyperactivity in patients with ADHD.
- FOCALIN should be used as a part of a total treatment program for ADHD that may include counseling or other therapies.

FOCALIN is a federally controlled substance (CII) because it contains dexmethylphenidate that can be a target for people who abuse prescription medicines or street drugs. Keep FOCALIN in a safe place to protect it from theft. Never give your FOCALIN to anyone else because it may cause death or harm them. Selling or giving away FOCALIN may harm others and is against the law.

Who should not take FOCALIN?

FOCALIN should not be taken if you or your child:

- are allergic to methylphenidate hydrochloride, or any of the ingredients in FOCALIN. See the end of this Medication Guide for a complete list of ingredients in FOCALIN.
- are taking or have taken within the past 14 days an anti-depression medicine called a monoamine oxidase inhibitor (MAOI).

FOCALIN may not be right for you or your child. Before starting FOCALIN, tell your or your child’s healthcare provider about all health conditions (or a family history of), including:

- heart problems, heart disease, heart defects, or high blood pressure
- mental problems, including psychosis, mania, bipolar illness, or depression
- circulation problems in fingers or toes
- have eye problems, including increased pressure in your eye, glaucoma, or problems with your close-up vision (farsightedness)
- have or had repeated movements or sounds (tics) or Tourette’s syndrome, or have a family history of tics or Tourette’s syndrome.
- if you are pregnant or plan to become pregnant. It is not known if FOCALIN will harm your unborn baby.
- There is a pregnancy registry for females who are exposed to ADHD medications, including FOCALIN during pregnancy. The purpose of the registry is to collect information about the health of females exposed to FOCALIN and their baby. If you or your child becomes pregnant during treatment with FOCALIN, talk to your healthcare provider about registering with the National Pregnancy Registry of ADHD medications at 1-866- 961-2388 or visit online at https://womensmentalhealth.org/adhd-medications/.
- if you are breastfeeding or plan to breastfeed. FOCALIN passes into your breast milk. Talk to your healthcare provider about the best way to feed the baby during treatment with FOCALIN.

Tell your healthcare provider about all of the medicines that you or your child takes, including prescription and over-the- counter medicines, vitamins, and herbal supplements. FOCALIN and some medicines may interact with each other and cause serious side effects. Sometimes the doses of other medicines will need to be adjusted while taking FOCALIN.

Your healthcare provider will decide whether FOCALIN can be taken with other medicines.

Especially tell your healthcare provider if you or your child takes:

- blood pressure medicines (anti-hypertensive)

Know the medicines that you or your child takes. Keep a list of your medicines with you to show your healthcare provider and pharmacist.

- You should not take FOCALIN on the day of your operation if a certain type of anesthetic is used. This is because there is a chance of a sudden rise in blood pressure and heart rate during the operation.

Do not start any new medicine while taking FOCALIN without talking to your healthcare provider first.

How should FOCALIN be taken?

- Take FOCALIN exactly as prescribed. Your healthcare provider may adjust the dose until it is right for you or your child.
- Take FOCALIN twice daily, at least 4 hours apart.
- FOCALIN may be taken with or without food.
- Your healthcare provider may do regular checks of the blood, heart, and blood pressure while taking FOCALIN.
- Children should have their height and weight checked often while taking FOCALIN. FOCALIN treatment may be stopped if a problem is found during these check-ups.

If you or your child take too much FOCALIN, call your healthcare provider or Poison Help line at 1-800-222-1222 or go to the nearest hospital emergency room right away.

What are the possible side effects of FOCALIN?

FOCALIN may cause serious side effects, including:

- see “What is the most important information I should know about FOCALIN?” for information on reported heart and mental problems.
- painful and prolonged erections (priapism) have occurred with methylphenidate. If you or your child develops priapism, seek medical help right away. Because of the potential for lasting damage, priapism should be evaluated by a healthcare provider immediately.
- circulation problems in fingers and toes (peripheral vasculopathy, including Raynaud’s phenomenon):
- fingers or toes may feel numb, cool, painful
- fingers or toes may change color from pale, to blue, to red

Tell your healthcare provider if you or your child have, numbness, pain, skin color change, or sensitivity to temperature in the fingers or toes.

- Call your healthcare provider right away if you have or your child has any signs of unexplained wounds appearing on fingers or toes while taking FOCALIN.
- Slowing of growth (height and weight) in children. Children should have their height and weight checked often during treatment with FOCALIN. FOCALIN treatment may be stopped if your child is not growing or gaining weight.
- Eye problems (increased pressure in the eye and glaucoma). Call your healthcare provider right away if you or your child develop changes in your vision or eye pain, swelling, or redness.
- New or worsening tics or worsening Tourette’s syndrome. Tell your healthcare provider if you or your child get any new or worsening tics or worsening Tourette’s syndrome during treatment with FOCALIN.
- Common side effects include:
  - abdominal pain
  - fever
  - anorexia
  - nausea

Call your doctor for medical advice about side effects. You may report side effects to FDA at 1-800-FDA-1088.

How should I store FOCALIN?

- Store FOCALIN in a safe place and in a tightly closed container at room temperature between 68°F to 77°F (20°C to 25°C).
- Protect from light and moisture.
- Dispose of remaining, unused, or expired FOCALIN by a medicine take-back program at a U.S. Drug Enforcement Administration (DEA) authorized collection site. If no take-back program or DEA authorized collector is available, mix FOCALIN with an undesirable, nontoxic substance, such as dirt, cat litter, or used coffee grounds to make it less appealing to children and pets. Place the mixture in a container, such as a sealed plastic bag and throw away FOCALIN in the household trash. Visit www.fda.gov/drugdisposal for additional information on disposal of unused medicines.
- Keep FOCALIN and all medicines out of the reach of children.

General information about the safe and effective use of FOCALIN.

Medicines are sometimes prescribed for purposes other than those listed in a Medication Guide. You can ask your pharmacist or healthcare provider for information about FOCALIN that is written for healthcare professionals. Do not use FOCALIN for a condition for which it was not prescribed. Do not give FOCALIN to other people, even if they have the same symptoms that you have. It may harm them and it is against the law.

What are the ingredients in FOCALIN?

Active ingredient: dexmethylphenidate hydrochloride

Inactive ingredients: FD&C blue no.1 #5516 aluminum lake (2.5 mg tablets), D&C yellow #10 aluminum lake (5 mg tablets), the 10 mg tablet contains no dye; lactose monohydrate, magnesium stearate, microcrystalline cellulose, pregelatinized starch, and sodium starch glycolate.

Manufactured by

Mikart, LLC, Atlanta, GA 30318 for

Sandoz Inc., Princeton, NJ 08540

For additional medication guide please go to www.us.sandoz.com or call 1-800-525-8747.

This Medication Guide has been approved by the U.S. Food and Drug Administration. Revised: 05/2024

PRINCIPAL DISPLAY PANEL

Sandoz NDC 66758-250-01

Focalin®

dexmethylphenidate
hydrochloride

2.5 mg

100 Tablets

Rx only

Dispense with Medication Guide
attached or provided separately.

PRINCIPAL DISPLAY PANEL

Sandoz NDC 66758-251-01

Focalin®

dexmethylphenidate
hydrochloride

5 mg

100 Tablets

Rx only

Dispense with Medication Guide
attached or provided separately.

PRINCIPAL DISPLAY PANEL

Sandoz NDC 66758-252-01

Focalin®

dexmethylphenidate
hydrochloride

10 mg

100 Tablets

Rx only

Dispense with Medication Guide
attached or provided separately.